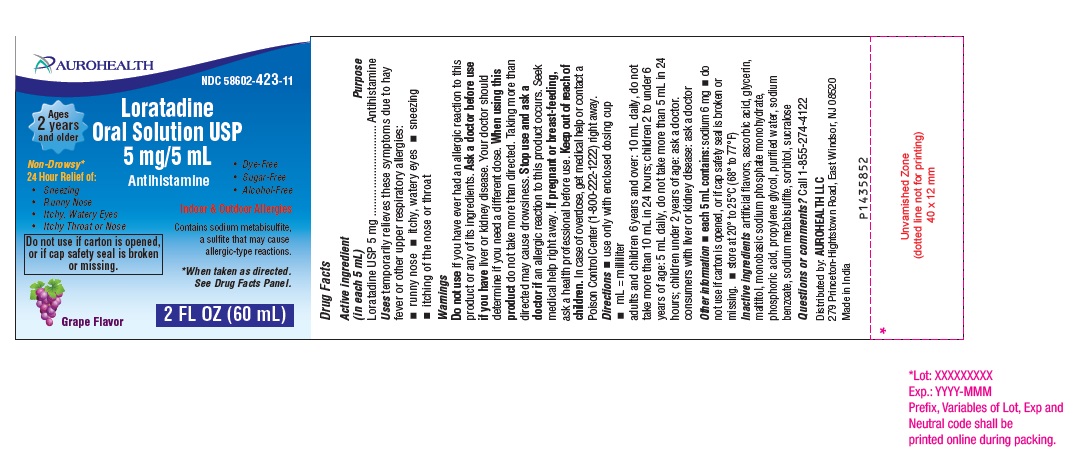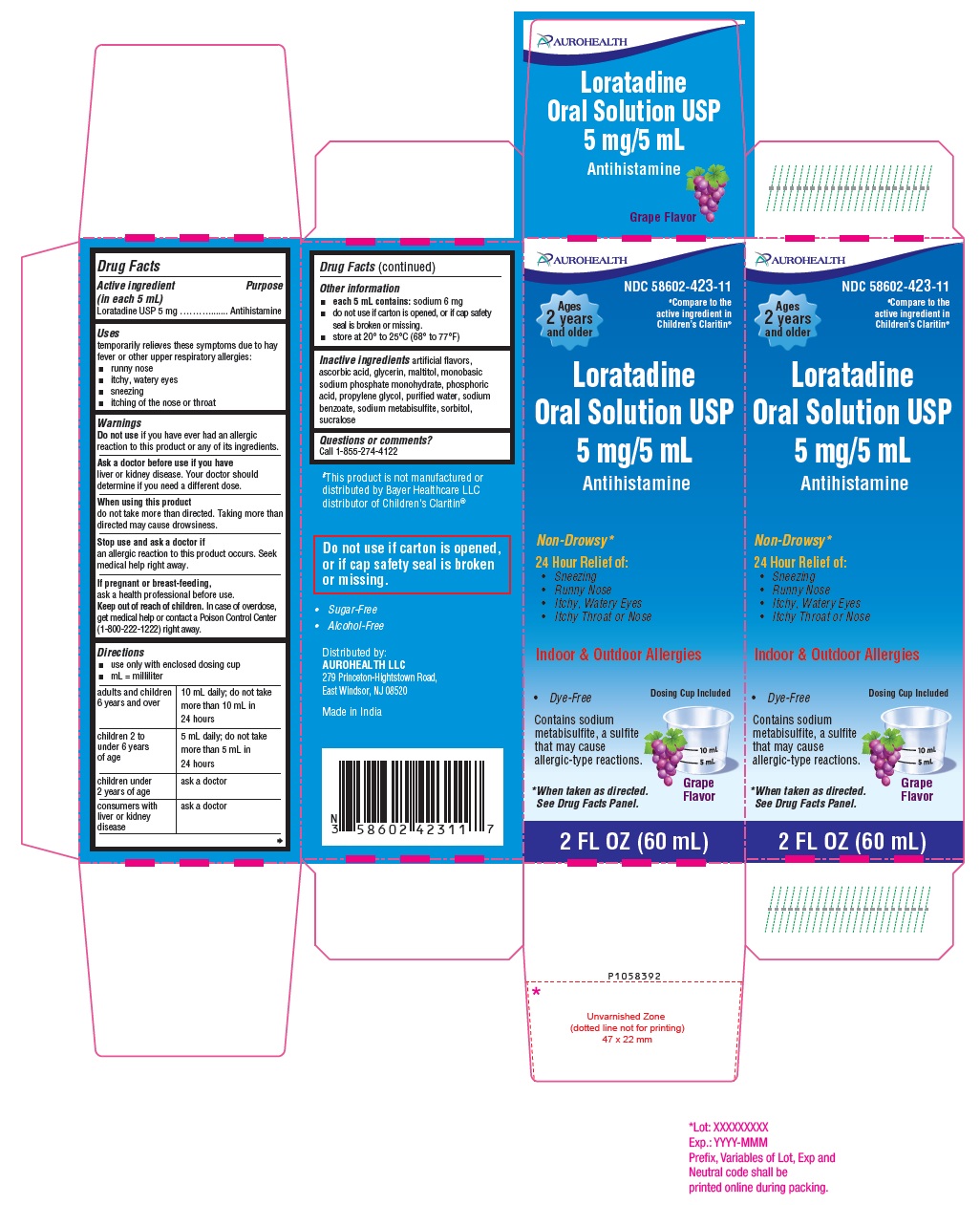 DRUG LABEL: Loratadine
NDC: 58602-423 | Form: SOLUTION
Manufacturer: Aurohealth LLC
Category: otc | Type: Human OTC Drug Label
Date: 20250120

ACTIVE INGREDIENTS: LORATADINE 5 mg/5 mL
INACTIVE INGREDIENTS: GRAPE; ASCORBIC ACID; GLYCERIN; MALTITOL; SODIUM PHOSPHATE, MONOBASIC, MONOHYDRATE; PHOSPHORIC ACID; PROPYLENE GLYCOL; WATER; SODIUM BENZOATE; SODIUM METABISULFITE; SORBITOL; SUCRALOSE

Loratadine Oral Solution USP 5 mg/5 mL

Drug Facts

Active ingredient (in each 5 mL)
Loratadine USP 5 mg

Purpose

Antihistamine

Uses

temporarily relieves these symptoms due to hay fever or other upper respiratory allergies:

- runny nose
- itchy, watery eyes
- sneezing
- itching of the nose or throat

Warnings

Do not use if you have ever had an allergic reaction to this product or any of its ingredients.

Ask a doctor before use if you have

liver or kidney disease. Your doctor should determine if you need a different dose.

When using this product

do not take more than directed. Taking more than directed may cause drowsiness.

Stop use and ask a doctor if

an allergic reaction to this product occurs. Seek medical help right away.

If pregnant or breast-feeding,

ask a health professional before use.

Keep out of reach of children.

In case of overdose, get medical help or contact a Poison Control Center (1-800-222-1222) right away.

Directions

- use only with enclosed dosing cup
- mL = milliliter

adults and children 6 years and over | 10 mL daily; do not take more than 10 mL in 24 hours
children 2 to under 6 years of age | 5 mL daily; do not take more than 5 mL in 24 hours
children under 2 years of age | ask a doctor
consumers with liver or kidney disease | ask a doctor

Other information

- each 5 mL contains: sodium 6 mg
- do not use if carton is opened, or if cap safety seal is broken or missing.
- store at 20° to 25°C (68° to 77°F)

Inactive ingredients

artificial flavors, ascorbic acid, glycerin, maltitol, monobasic sodium phosphate monohydrate, phosphoric acid, propylene glycol, purified water, sodium benzoate, sodium metabisulfite, sorbitol, sucralose.

Questions or comments?

Call 1-855-274-4122
Distributed by:
AUROHEALTH LLC
279 Princeton-Hightstown Road,
East Windsor, NJ 08520
Made in India

PACKAGE LABEL-PRINCIPAL DISPLAY PANEL - 5 mg/5 mL (60 mL Bottle)

AUROHEALTH
NDC 58602-423-11
Ages
2 years
and older

Loratadine
Oral Solution USP
5 mg/5 mL
Antihistamine
Non-Drowsy*
24 Hour Relief of:

- Sneezing
- Runny Nose
- Itchy, Watery Eyes
- Itchy Throat or Nose

Do not use if carton is opened,
or if cap safety seal is broken
or missing.

- Dye-Free
- Sugar-Free
- Alcohol Free

Indoor & Outdoor Allergies

Contains sodium metabisulfite,
a sulfite that may cause
allergic-type reactions.

* When taken as directed.
See Drug Facts Panel.
Grape Flavor
2 FL OZ (60 mL)

PACKAGE LABEL-PRINCIPAL DISPLAY PANEL - 5 mg/5 mL Carton (60 mL)

AUROHEALTH
NDC 58602-423-11
#Compare to the
active ingredient in
children’s Claritin®
Ages

2 years
and older
Loratadine
Oral Solution USP
5 mg/5 mL
Antihistamine
Non-Drowsy*
24 Hour Relief of:

- Sneezing
- Runny Nose
- Itchy,watery Eyes
- Itchy Throat or Nose

Indoor & Outdoor Allergies
Dosing Cup Included

- Dye-Free

Contains sodium
metabisulfite, a sulfite
that may cause
allergic-type reactions.

* When taken as directed.

See Drug Facts Panel.
Grape

Flavor
2 FL OZ (60 mL)